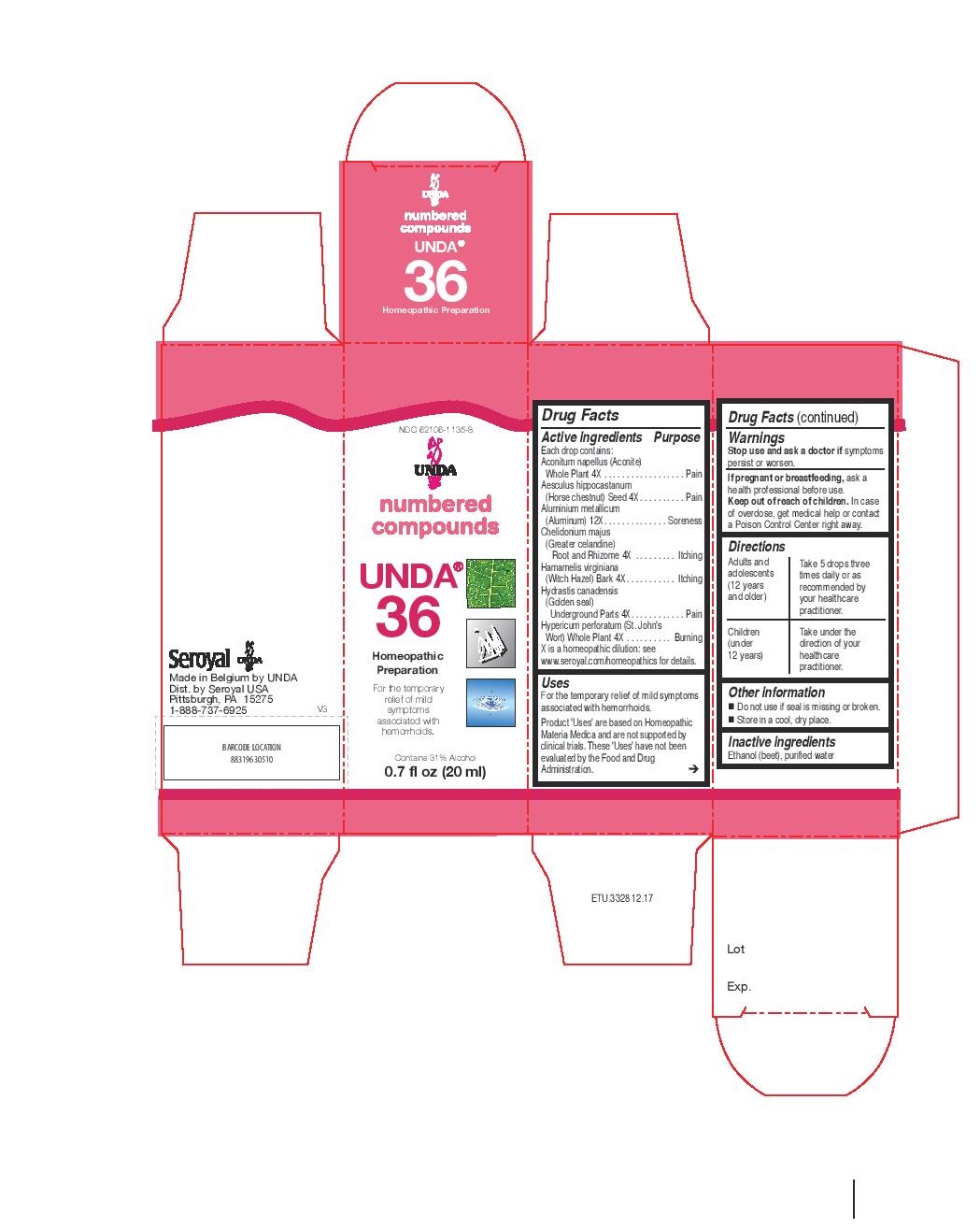 DRUG LABEL: Unda 36
NDC: 62106-1135 | Form: LIQUID
Manufacturer: Seroyal USA
Category: homeopathic | Type: HUMAN OTC DRUG LABEL
Date: 20221109

ACTIVE INGREDIENTS: ACONITUM NAPELLUS 4 [hp_X]/20 mL; HORSE CHESTNUT 4 [hp_X]/20 mL; ALUMINUM 12 [hp_X]/20 mL; CHELIDONIUM MAJUS ROOT 4 [hp_X]/20 mL; HAMAMELIS VIRGINIANA BARK 4 [hp_X]/20 mL; GOLDENSEAL 4 [hp_X]/20 mL; HYPERICUM PERFORATUM 4 [hp_X]/20 mL
INACTIVE INGREDIENTS: ALCOHOL; WATER

Unda 36

Active ingredients

Each drop contains:
Aconitum napellus (Aconite) Whole Plant 4X
Aesculus hippocastanum (Horse chestnut) Seed 4X
Aluminium metallicum (Aluminum) 12X
Chelidonium majus (Greater celandine) Root and Rhizome 4X
Hamamelis virginiana (Witch Hazel) Bark 4X
Hydrastis canadensis (Golden seal) Underground Parts 4X
Hypericum perforatum (St. John's Wort) Whole Plant 4X

Uses
For the temporary relief of mild symptoms associated with hemorrhoids.

Warnings
Stop use and ask a doctor if symptoms persist or worsen.
If pregnant or breastfeeding, ask a health professional before use.
Keep out of reach of children.

In case of overdose, get medical help or contact a Poison Control Center right away.

Stop use and ask a doctor if symptoms persist or worsen.

PREGNANCY OR BREAST FEEDING

If pregnant or breastfeeding, ask a health professional before use.

Keep out of reach of children.

OVERDOSAGE

In case of overdose, get medical help or contact a Poison Control Center right away.

Inactive ingredients
Ethanol (beet), purified water

Other information
Do not use if seal is missing or broken.
Store in a cool, dry place.

Directions
Adults and adolescents (12 years and older)

Take 5 drops three times daily or as recommended by your healthcare practitioner.

Children (under 12 years)

Take under the direction of your healthcare practitioner.

Uses
For the temporary relief of mild symptoms associated with hemorrhoids.

Directions
Adults and adolescents (12 years and older)

Take 5 drops three times daily or as recommended by your healthcare practitioner.

Children (under 12 years)

Take under the direction of your healthcare practitioner.

PACKAGE LABEL

NDC 62106-1135-8

UNDA

numbered compounds

UNDA 36

Homeopathic Preparation

For the temporary relief of mild symptoms

associated with hemorrhoids.

Contains 31% Alcohol
0.7 fl oz (20 ml)